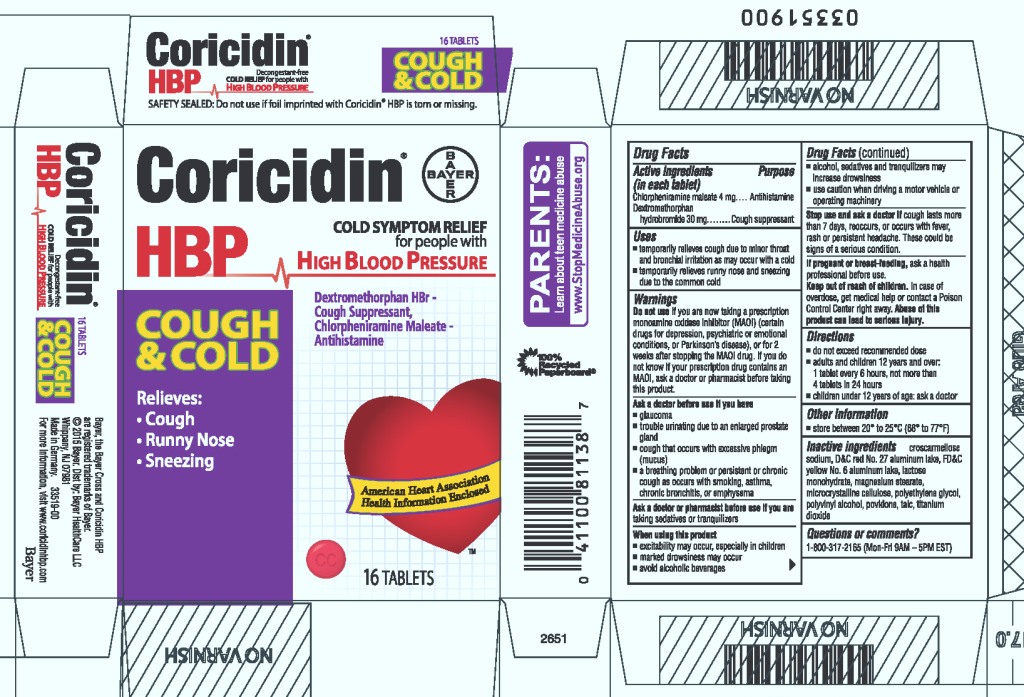 DRUG LABEL: Coricidin HBP Cough and Cold
NDC: 11523-4326 | Form: TABLET, FILM COATED
Manufacturer: Bayer HealthCare LLC.
Category: otc | Type: HUMAN OTC DRUG LABEL
Date: 20251205

ACTIVE INGREDIENTS: CHLORPHENIRAMINE MALEATE 4 mg/1 1; DEXTROMETHORPHAN HYDROBROMIDE 30 mg/1 1
INACTIVE INGREDIENTS: CROSCARMELLOSE SODIUM; D&C RED NO. 27; FD&C YELLOW NO. 6; ALUMINUM OXIDE; LACTOSE MONOHYDRATE; MAGNESIUM STEARATE; CELLULOSE, MICROCRYSTALLINE; POLYETHYLENE GLYCOL, UNSPECIFIED; POLYVINYL ALCOHOL; POVIDONE; TALC; TITANIUM DIOXIDE

Coricidin® HBP Cough and Cold

Drug Facts

ACTIVE INGREDIENT

Active ingredients (in each tablet) | Purpose
Chlorpheniramine maleate 4 mg | Antihistamine
Dextromethorphan hydrobromide 30 mg | Cough suppressant

Uses

- temporarily relieves cough due to minor throat and bronchial irritation as may occur with a cold
- temporarily relieves runny nose and sneezing due to the common cold

Warnings

Do not use if you are now taking a prescription monoamine oxidase inhibitor (MAOI) (certain drugs for depression, psychiatric or emotional conditions, or Parkinson's disease), or for 2 weeks after stopping the MAOI drug. If you do not know if your prescription drug contains an MAOI, ask a doctor or pharmacist before taking this product.

Ask a doctor before use if you have

- glaucoma
- trouble urinating due to an enlarged prostate gland
- cough that occurs with excessive phlegm (mucus)
- a breathing problem or persistent or chronic cough as occurs with smoking, asthma, chronic bronchitis, or emphysema

Ask a doctor or pharmacist before use if you are

taking sedatives or tranquilizers

When using this product

- excitability may occur, especially in children
- marked drowsiness may occur
- avoid alcoholic beverages
- alcohol, sedatives and tranquilizers may increase drowsiness
- use caution when driving a motor vehicle or operating machinery

Stop use and ask a doctor if cough lasts more than 7 days, reoccurs, or occurs with fever, rash or persistent headache. These could be signs of a serious condition.

PREGNANCY OR BREAST FEEDING

If pregnant or breast-feeding, ask a health professional before use.

Keep out of reach of children. In case of overdose, get medical help or contact a Poison Control Center right away. Abuse of this product can lead to serious injury.

Directions

- do not exceed recommended dose
- adults and children 12 years and over:
  1 tablet every 6 hours, not more often than
  4 tablets in 24 hours
- children under 12 years of age: ask a doctor

Other information

- store between 20° to 25°C (68° to 77°F)

Inactive ingredients

croscarmellose sodium, D&C red No. 27 aluminum lake, FD&C yellow No. 6 aluminum lake, lactose monohydrate, magnesium stearate, microcrystalline cellulose, polyethylene glycol, polyvinyl alcohol, povidone, talc, titanium dioxide

Questions or comments?

Call 1-800-317-2165 (Mon-Fri 9AM-5PM EST)

PRINCIPAL DISPLAY PANEL - 16 Tablet Carton

Coricidin®
HBP

Decongestant-free
COLD SYMPTOM RELIEF for people with
HIGH BLOOD PRESSURE

Dextromethorphan HBr-Cough Suppressant,
Chlorpheniramine Maleate-Antihistamine

COUGH
&COLD

Relieves:

- Cough
- Runny Nose
- Sneezing

16 TABLETS